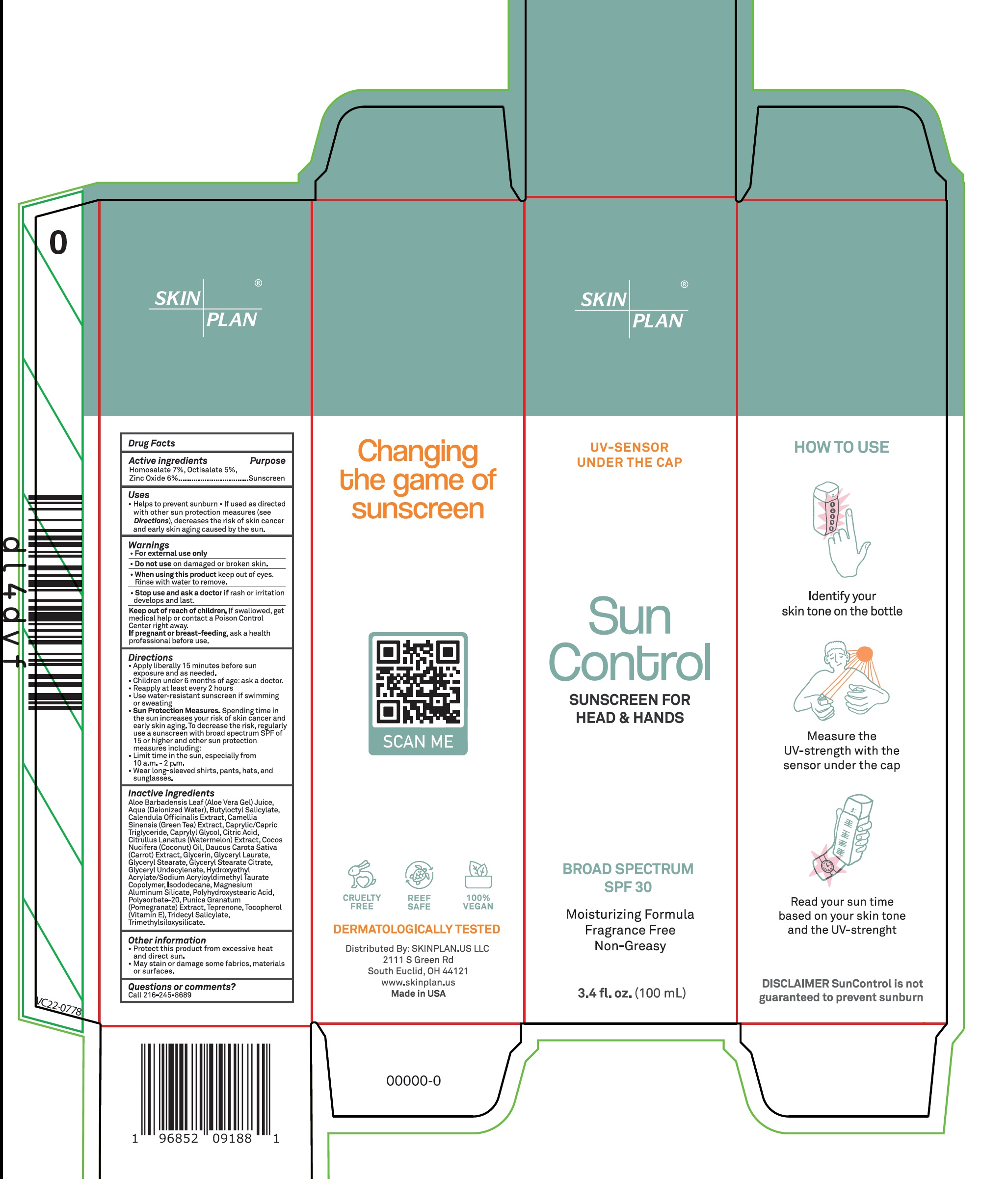 DRUG LABEL: SUN CONTROL BROAD SPECTRUM SPF 30
NDC: 84259-475 | Form: CREAM
Manufacturer: SKINPLAN.US LLC
Category: otc | Type: HUMAN OTC DRUG LABEL
Date: 20240415

ACTIVE INGREDIENTS: HOMOSALATE 70 mg/1 mL; OCTISALATE 50 mg/1 mL; ZINC OXIDE 60 mg/1 mL
INACTIVE INGREDIENTS: ALOE VERA LEAF; WATER; BUTYLOCTYL SALICYLATE; CALENDULA OFFICINALIS FLOWER; GREEN TEA LEAF; MEDIUM-CHAIN TRIGLYCERIDES; CAPRYLYL GLYCOL; CITRIC ACID MONOHYDRATE; WATERMELON; COCONUT OIL; CARROT; GLYCERIN; GLYCERYL LAURATE; GLYCERYL MONOSTEARATE; GLYCERYL STEARATE CITRATE; ISODODECANE; MAGNESIUM ALUMINUM SILICATE; TEPRENONE; .ALPHA.-TOCOPHEROL; TRIDECYL SALICYLATE

SUN CONTROL BROAD SPECTRUM SPF-30

Active ingredients

Homosalate 7%,

Octisalate 5%,

Zinc oxide 6%

Purpose

Sunscreen

Uses

- Helps to prevent sunburn
- If used as directed with other sun protection measures (see Directions), decreases the risk of skin cancer and early skin aging caused by the sun.

Warnings

- For external use only

• Do not use

on damaged or broken skin.

• When using this product

keep out of eyes. Rinse with water to remove.

• Stop use and ask a doctor if

rash or irritation develops and last.

Keep out of reach of children.

If swallowed, get medical help or contact a Poison Control Center right away

If pregnant or breast-feeding,

ask a health professional before use.

Directions

- Apply liberally 15 minutes before sun exposure and as needed.
- Children under 6 months of age: ask a doctor.
- Reapply at least every 2 hours
- Use water-resistant sunscreen if swimming or sweating
- Sun Protection Measures.Spending time in the sun increases your risk of skin cancer and early skin aging. To decrease the risk, regularly use a sunscreen with broad spectrum SPF of 15 or higher and other sun protection measures including:
- Limit time in the sun, especially from 10 a.m. - 2 p.m.
- Wear long-sleeved shirts, pants, hats, and sunglasses.

Inactive ingredients

Aloe Barbadensis Leaf (Aloe Vera Gel) Juice, Aqua (Deionized Water), Butyloctyl Salicylate, Calendula Officinalis Extract, Camellia Sinensis (Green Tea) Extract, Caprylic/Capric Triglyceride, Caprylyl Glycol, Citric Acid, Citrullus Lanatus (Watermelon) Extract, Cocos Nucifera (Coconut) Oil, Daucus Carota Sativa (Carrot) Extract, Glycerin, Glyceryl Laurate, Glyceryl Stearate, Glyceryl Stearate Citrate, Glyceryl Undecylenate, Hydroxyethyl Acrylate/Sodium Acryloyldimethyl Taurate Copolymer, Isododecane, Magnesium Aluminum Silicate, Polyhydroxystearic Acid, Polysorbate-20, Punica Granatum (Pomegranate) Extract, Teprenone, Tocopherol (Vitamin E), Tridecyl Salicylate, Trimethylsiloxysilicate.

Other information

- Protect this product from excessive heat and direct sun.
- May stain or damage some fabrics, materials or surfaces.

Questions or comments?

Call 216-245-8689